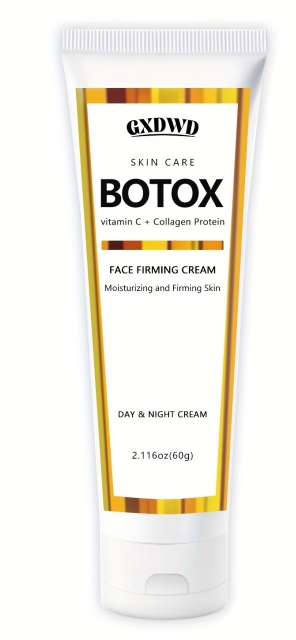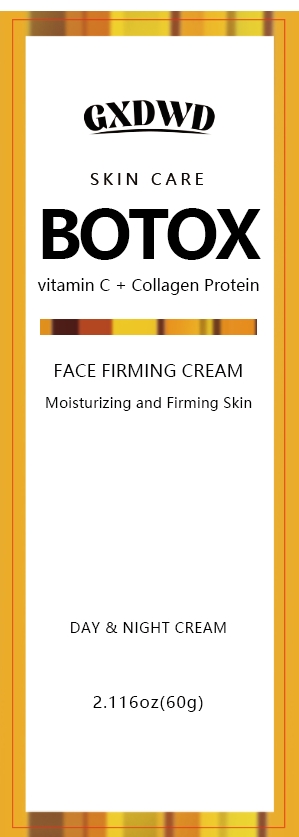 DRUG LABEL: face cream
NDC: 84025-178 | Form: CREAM
Manufacturer: Guangzhou Yanxi Biotechnology Co.. Ltd
Category: otc | Type: HUMAN OTC DRUG LABEL
Date: 20240902

ACTIVE INGREDIENTS: CETEARYL OLIVATE 3 mg/60 g; NIACINAMIDE 5 mg/60 g
INACTIVE INGREDIENTS: WATER

WARNINGS

keep out of children

DOSAGE AND ADMINISTRATION

Cream for moisturizing and firming facial skin

INACTIVE INGREDIENT

AQUA

INDICATIONS AND USAGE

For daily skin care

keep out of children

PURPOSE

Effectively moisturizes and cares for the skin